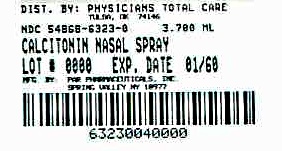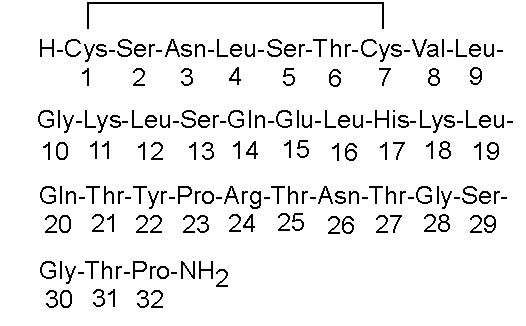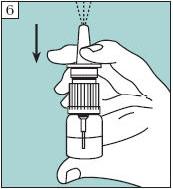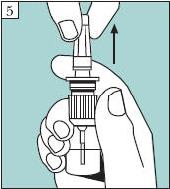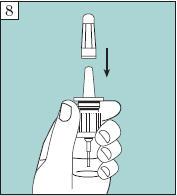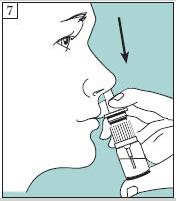 DRUG LABEL: CALCITONIN SALMON
                        
NDC: 54868-6323 | Form: SPRAY, METERED
Manufacturer: Physicians Total Care, Inc.
Category: prescription | Type: HUMAN PRESCRIPTION DRUG LABEL
Date: 20111212

ACTIVE INGREDIENTS: CALCITONIN SALMON 200 [iU]/0.09 mL
INACTIVE INGREDIENTS: HYDROCHLORIC ACID; NITROGEN; SODIUM CHLORIDE; WATER

Calcitonin-Salmon
Nasal Spray, USP
Rx Only
Prescribing Information

DESCRIPTION

Calcitonin is a polypeptide hormone secreted by the parafollicular cells of the thyroid gland in mammals and by the ultimobranchial gland of birds and fish.

Calcitonin-Salmon Nasal Spray is a synthetic polypeptide of 32 amino acids in the same linear sequence that is found in calcitonin of salmon origin. This is shown by the following graphic formula:

It is provided in 3.7 mL fill glass bottles as a solution for nasal administration. This is sufficient medication for at least 30 doses.

Active Ingredient:calcitonin-salmon, 2200 I.U. per mL (corresponding to 200 I.U. per 0.09 mL actuation).

Inactive Ingredients:sodium chloride, chlorobutanol, hydrochloric acid (added as necessary to adjust pH), purified water and nitrogen.

The activity of Calcitonin-Salmon Nasal Spray is stated in International Units based on bioassay in comparison with the International Reference Preparation of calcitonin-salmon for Bioassay, distributed by the National Institute of Biologic Standards and Control, Holly Hill, London.

CLINICAL PHARMACOLOGY

Calcitonin acts primarily on bone, but direct renal effects and actions on the gastrointestinal tract are also recognized. Calcitonin-salmon appears to have actions essentially identical to calcitonins of mammalian origin, but its potency per mg is greater and it has a longer duration of action.

The information below, describing the clinical pharmacology of calcitonin, has been derived from studies with injectable calcitonin. The mean bioavailability of Calcitonin-Salmon Nasal Spray is approximately 3% of that of injectable calcitonin in normal subjects and, therefore, the conclusions concerning the clinical pharmacology of this preparation may be different.

The actions of calcitonin on bone and its role in normal human bone physiology are still not completely elucidated, although calcitonin receptors have been discovered in osteoclasts and osteoblasts.

Single injections of calcitonin cause a marked transient inhibition of the ongoing bone resorptive process. With prolonged use, there is a persistent, smaller decrease in the rate of bone resorption. Histologically, this is associated with a decreased number of osteoclasts and an apparent decrease in their resorptive activity. In vitro studies have shown that calcitonin-salmon causes inhibition of osteoclast function with loss of the ruffled osteoclast border responsible for resorption of bone. This activity resumes following removal of calcitonin-salmon from the test system. There is some evidence from the in vitro studies that bone formation may be augmented by calcitonin through increased osteoblastic activity.

Animal studies indicate that endogenous calcitonin, primarily through its action on bone, participates with parathyroid hormone in the homeostatic regulation of blood calcium. Thus, high blood calcium levels cause increased secretion of calcitonin which, in turn, inhibits bone resorption. This reduces the transfer of calcium from bone to blood and tends to return blood calcium towards the normal level. The importance of this process in humans has not been determined. In normal adults, who have a relatively low rate of bone resorption, the administration of exogenous calcitonin results in only a slight decrease in serum calcium in the limits of the normal range. In normal children and in patients with Paget’s disease in whom bone resorption is more rapid, decreases in serum calcium are more pronounced in response to calcitonin.

Bone biopsy and radial bone mass studies at baseline and after 26 months of daily injectable calcitonin indicate that calcitonin therapy results in formation of normal bone.

Postmenopausal Osteoporosis

Osteoporosis is a disease characterized by low bone mass and architectural deterioration of bone tissue leading to enhanced bone fragility and a consequent increase in fracture risk as patients approach or fall below a bone mineral density associated with increased frequency of fracture. The most common type of osteoporosis occurs in postmenopausal females. Osteoporosis is a result of a disproportionate rate of bone resorption compared to bone formation which disrupts the structural integrity of bone, rendering it more susceptible to fracture. The most common sites of these fractures are the vertebrae, hip, and distal forearm (Colles’ fractures). Vertebral fractures occur with the highest frequency and are associated with back pain, spinal deformity and a loss of height.

Calcitonin-Salmon Nasal Spray, given by the intranasal route, has been shown to increase spinal bone mass in post-menopausal women with established osteoporosis but not in early postmenopausal women.

Calcium Homeostasis

In two clinical studies designed to evaluate the pharmacodynamic response to Calcitonin-Salmon Nasal Spray, administration of 100-1600 I.U. to healthy volunteers resulted in rapid and sustained small decreases (but still within the normal range) in both total serum calcium and serum ionized calcium. Single doses greater than 400 I.U. did not produce any further biological response to the drug. The development of hypocalcemia has not been reported in studies in healthy volunteers or postmenopausal females.

Kidney

Studies with injectable calcitonin show increases in the excretion of filtered phosphate, calcium, and sodium by decreasing their tubular reabsorption. Comparable studies have not been carried out with Calcitonin-Salmon Nasal Spray.

Gastrointestinal Tract

Some evidence from studies with injectable preparations suggest that calcitonin may have significant actions on the gastrointestinal tract. Short-term administration of injectable calcitonin results in marked transient decreases in the volume and acidity of gastric juice and in the volume and the trypsin and amylase content of pancreatic juice. Whether these effects continue to be elicited after each injection of calcitonin during chronic therapy has not been investigated. These studies have not been conducted with Calcitonin-Salmon Nasal Spray.

Pharmacokinetics and Metabolism

The bioavailability of Calcitonin-Salmon Nasal Spray relative to intramuscular administration is between 3 and 5%. Calcitonin-Salmon Nasal Spray is absorbed by the nasal mucosa with a mean Tmax of about 13 minutes. The terminal half-life of calcitonin-salmon has been calculated to be around 18 minutes and no evidence of accumulation was observed with multiple dosing. Plasma exposure was higher following administration of 400 IU nasal spray compared to that after 200 IU dose. As is the case with other polypeptide hormones, there is very little value in monitoring plasma levels of salmon calcitonin since these are not directly predictive of the therapeutic response. Hence, Calcitonin-Salmon activity should be evaluated by using clinical parameters of efficacy.

INDICATIONS AND USAGE

Postmenopausal Osteoporosis

Calcitonin-Salmon Nasal Spray is indicated for the treatment of postmenopausal osteoporosis in females greater than 5 years postmenopause with low bone mass relative to healthy premenopausal females. Calcitonin-Salmon Nasal Spray should be reserved for patients who refuse or cannot tolerate estrogens or in whom estrogens are contraindicated. Use of Calcitonin-Salmon Nasal Spray is recommended in conjunction with an adequate calcium (at least 1000 mg elemental calcium per day) and vitamin D (400 I.U. per day) intake to retard the progressive loss of bone mass. The evidence of efficacy is based on increases in spinal bone mineral density observed in clinical trials.

Two randomized, placebo controlled trials were conducted in 325 postmenopausal females [227 Calcitonin-Salmon Nasal Spray treated and 98 placebo treated] with spinal, forearm or femoral bone mineral density (BMD) at least one standard deviation below normal for healthy premenopausal females. These studies conducted over two years demonstrated that 200 I.U. daily of Calcitonin-Salmon Nasal Spray increases lumbar vertebral BMD relative to baseline and relative to placebo in osteoporotic females who were greater than 5 years postmenopause. Calcitonin-Salmon Nasal Spray produced statistically significant increases in lumbar vertebral BMD compared to placebo as early as 6 months after initiation of therapy with persistence of this level for up to 2 years of observation.

No effects of Calcitonin-Salmon Nasal Spray on cortical bone of the forearm or hip were demonstrated. However, in one study, BMD of the hip showed a statistically significant increase compared with placebo in a region composed of predominantly trabecular bone after 1 year of treatment changing to a trend at 2 years that was no longer statistically significant.

CONTRAINDICATIONS

Clinical allergy to calcitonin-salmon

WARNINGS

Allergic Reactions

Because calcitonin is a polypeptide, the possibility of a systemic allergic reaction exists. A few cases of serious allergic-type reactions have been reported in patients receiving Calcitonin-Salmon Nasal Spray, including cases of anaphylaxis and anaphylactic shock. With injectable calcitonin-salmon there have been a few reports of serious allergic-type reactions (e.g., bronchospasm, swelling of the tongue or throat, anaphylactic shock), including very rare reports of death attributed to anaphylaxis. The usual provisions should be made for the emergency treatment of such a reaction should it occur. Allergic reactions should be differentiated from generalized flushing and hypotension.

For patients with suspected sensitivity to calcitonin, skin testing should be considered prior to treatment utilizing a dilute, sterile solution of calcitonin-salmon injection. Physicians may wish to refer patients who require skin testing to an allergist. A detailed skin testing protocol is available from the Drug Safety Department of Par Pharmaceutical Companies Inc. at 1-800-828-9393.

PRECAUTIONS

Drug Interactions

Formal studies designed to evaluate drug interactions with calcitonin-salmon have not been done. No drug interaction studies have been performed with Calcitonin-Salmon Nasal Spray ingredients.

Concomitant use of calcitonin and lithium may lead to a reduction in plasma lithium concentrations due to increased urinary clearance of lithium. The dose of lithium may need to be adjusted.

The effects of prior use of diphosphonates in postmenopausal osteoporosis patients have not been assessed; however, in patients with Paget’s disease, prior diphosphonate use appears to reduce the anti-resorptive response to Calcitonin-Salmon Nasal Spray.

Periodic nasal examinations with visualization of the nasal mucosa, turbinates, septum and mucosal blood vessel status are recommended.

The development of mucosal alterations or transient nasal conditions occurred in up to 9% of patients who received Calcitonin-Salmon Nasal Spray and in up to 12% of patients who received placebo nasal spray in studies in postmenopausal females. The majority of patients (approximately 90%) in whom nasal abnormalities were noted also reported nasally related complaints/symptoms as adverse events. Therefore, a nasal examination should be performed prior to start of treatment with nasal calcitonin and at any time nasal complaints occur.

In all postmenopausal patients treated with Calcitonin-Salmon Nasal Spray, the most commonly reported nasal adverse events included rhinitis (12%), epistaxis (3.5%), and sinusitis (2.3%). Smoking was shown not to have any contributory effect on the occurrence of nasal adverse events. One patient (0.3%) treated with Calcitonin-Salmon Nasal Spray who was receiving 400 I.U. daily developed a small nasal wound. In clinical trials in another disorder (Paget’s disease), 2.8% of patients developed nasal ulcerations.

If severe ulceration of the nasal mucosa occurs, as indicated by ulcers greater than 1.5 mm in diameter or penetrating below the mucosa, or those associated with heavy bleeding, Calcitonin-Salmon Nasal Spray should be discontinued. Although smaller ulcers often heal without withdrawal of Calcitonin-Salmon Nasal Spray, medication should be discontinued temporarily until healing occurs.

Information for Patients

Careful instructions on pump assembly, priming of the pump and nasal introduction of Calcitonin-Salmon Nasal Spray should be given to the patient. Although instructions for patients are supplied with individual bottles, procedures for use should be demonstrated to each patient. Patients should notify their physician if they develop significant nasal irritation.

Patients should be advised of the following:

- Store new, unassembled bottles in the refrigerator between 2°C-8°C (36°F-46°F).
- Protect the product from freezing.
- Before priming the pump and using a new bottle, allow it to reach room temperature.
- Store bottle in use at room temperature 20°C to 25°C (68°F to 77°F) in an upright position, for up to 35 days. Each bottle contains at least 30 doses.
- See DOSAGE AND ADMINISTRATION, Priming (Activation) of Pump for complete instructions on priming the pump and administering Calcitonin-Salmon Nasal Spray.

You should keep track of the number of doses used from the bottle.

After 30 doses, each spray may not deliver the correct amount of medication, even if the bottle is not completely empty.

Carcinogenicity and Mutagenicity and Impairment of Fertility

An increased incidence of non-functioning pituitary adenomas has been observed in one-year toxicity studies in Sprague-Dawley and Fischer 344 Rats administered (subcutaneously) calcitonin-salmon at dosages of 80 I.U. per kilogram per day (16-19 times the recommended human parenteral dose and about 130-160 times the human intranasal dose based on body surface area). The findings suggest that calcitonin-salmon reduced the latency period for development of pituitary adenomas that do not produce hormones, probably through the perturbation of physiologic processes involved in the evolution of this commonly occurring endocrine lesion in the rat. Although administration of calcitonin- salmon reduces the latency period of the development of nonfunctional proliferative lesions in rats, it did not induce the hyperplastic/neoplastic process.

Calcitonin-salmon was tested for mutagenicity using Salmonella typhimurium (5 strains) and Escherichia coli (2 strains), with and without rat liver metabolic activation, and found to be non-mutagenic. The drug was also not mutagenic in a chromosome aberration test in mammalian V79 cells of the Chinese Hamster in vitro.

Laboratory Tests

Urine sediment abnormalities have not been reported in ambulatory volunteers treated with Calcitonin-Salmon Nasal Spray. Coarse granular casts containing renal tubular epithelial cells were reported in young adult volunteers at bed rest who were given injectable calcitonin-salmon to study the effect of immobilization on osteoporosis. There was no evidence of renal abnormality and the urine sediment became normal after calcitonin was stopped. Periodic examinations of urine sediment should be considered.

Pregnancy

Teratogenic Effects

Category C

Calcitonin-salmon has been shown to cause a decrease in fetal birth weights in rabbits when given by injection in doses 8-33 times the parenteral dose and 70-278 times the intranasal dose recommended for human use based on body surface area.

Since calcitonin does not cross the placental barrier, this finding may be due to metabolic effects on the pregnant animal. There are no adequate and well controlled studies in pregnant women with calcitonin-salmon. Calcitonin-Salmon Nasal Spray is not indicated for use in pregnancy.

Nursing Mothers

It is not known whether this drug is excreted in human milk. As a general rule, nursing should not be undertaken while a patient is on this drug since many drugs are excreted in human milk. Calcitonin has been shown to inhibit lactation in animals.

Pediatric Use

There are no data to support the use of Calcitonin-Salmon Nasal Spray in children. Disorders of bone in children referred to as idiopathic juvenile osteoporosis have been reported rarely. The relationship of these disorders to postmenopausal osteoporosis has not been established and experience with the use of calcitonin in these disorders is very limited.

Geriatric Use

In one large multi-centered, double-blind, randomized clinical study of Calcitonin-Salmon Nasal Spray, 279 patients were less than 65 years old, while 467 patients were 65 to 74 years old and 196 patients were 75 and over. Compared to subjects less than 65 years old, the incidence of nasal adverse events (rhinitis, irritation, erythema, and excoriation) was higher in patients over the age of 65, particularly those over the age of 75. Most events were mild in intensity. Other reported clinical experience has not identified differences in responses between the elderly and younger patients, but greater sensitivity of some older individuals cannot be ruled out.

ADVERSE REACTIONS

The incidence of adverse reactions reported in studies involving postmenopausal osteoporotic patients chronically exposed to Calcitonin-Salmon Nasal Spray (N=341) and to placebo nasal spray (N=131) and reported in greater than 3% of Calcitonin-Salmon Nasal Spray treated patients are presented below in the following table. Most adverse reactions were mild to moderate in severity. Nasal adverse events were most common with 70% mild, 25% moderate, and 5% severe in nature (placebo rates were 71% mild, 27% moderate, and 2% severe).

Adverse Reactions Occurring in at Least 3%Of Postmenopausal Patients Treated Chronically
Calcitonin-Salmon
 | Nasal Spray N = 341 | Placebo N = 131
Adverse Reaction | % of Patients | % of Patients
Rhinitis | 12.0 | 6.9
Symptom of Nose† | 10.6 | 16.0
Back Pain | 5.0 | 2.3
Arthralgia | 3.8 | 5.3
Epistaxis | 3.5 | 4.6
Headache | 3.2 | 4.6
† Symptom of nose includes: nasal crusts, dryness, redness or erythema, nasal sores, irritation, itching, thick feeling, soreness, pallor, infection, stenosis, runny/blocked, small wound, bleeding wound, tenderness, uncomfortable feeling and sore across bridge of nose.

Body as a whole – General Disorders: influenza-like symptoms*, fatigue*, edema (facial, peripheral and generalized), fever

Integumentary: erythematous rash*, skin ulceration, eczema, alopecia, pruritus, increased sweating

Musculoskeletal/Collagen: arthrosis*, myalgia*, arthritis, polymyalgia rheumatica, stiffness

Respiratory/Special Senses: sinusitis*, upper respiratory tract infection*, bronchospasm*, pharyngitis, bronchitis, pneumonia, coughing, dyspnea, taste perversion, parosmia, nasal congestion, sneezing, allergic rhinitis, nasal odor, mucosal excoriation, rhinitis ulcerative

Cardiovascular: hypertension*, angina pectoris*, tachycardia, palpitation, bundle branch block, myocardial infarction

Gastrointestinal: dyspepsia*, constipation*, abdominal pain*, nausea*, diarrhea*, vomiting, flatulence, increased appetite, gastritis, dry mouth

Liver/Metabolic: cholelithiasis, hepatitis, thirst, weight increase

Endocrine: goiter, hyperthyroidism

Urinary System: cystitis*, pyelonephritis, hematuria, renal calculus

Central and Peripheral Nervous System: dizziness*, paresthesia*, vertigo, migraine, neuralgia, agitation

Hearing/Vestibular: tinnitus, hearing loss, earache

Vision: abnormal lacrimation*, conjunctivitis*, blurred vision, vitreous floater, visual disturbance

Vascular: flushing, cerebrovascular accident, thrombophlebitis

Hematologic/Resistance Mechanisms: lymphadenopathy*, infection*, anemia

Psychiatric: depression*, insomnia, anxiety, anorexia

Immune system disorders: Hypersensitivity, anaphylaxis and anaphylactic shock

Common adverse reactions associated with the use of injectable calcitonin-salmon occurred less frequently in patients treated with Calcitonin-Salmon Nasal Spray than in those patients treated with injectable calcitonin. Nausea, with or without vomiting, which occurred in 1.8% of patients treated with the nasal spray (and 1.5% of those receiving placebo nasal spray) occurs in about 10% of patients who take injectable calcitonin-salmon. Flushing, which occurred in less than 1% of patients treated with the nasal spray, occurs in 2%-5% of patients treated with injectable calcitonin-salmon. Although the administered dosages of injectable and nasal spray calcitonin-salmon are comparable (50-100 units daily of injectable versus 200 units daily of nasal spray), the nasal dosage form has a mean bioavailability of about 3% (range 0.3%-30.6%) and therefore provides less drug to the systemic circulation, possibly accounting for the decrease in frequency of adverse reactions.

The collective foreign marketing experience with Calcitonin-Salmon Nasal Spray does not show evidence of any notable difference in the incidence profile of reported adverse reactions when compared with that seen in the clinical trials.

OVERDOSAGE

No instances of overdose with Calcitonin-Salmon Nasal Spray have been reported and no serious adverse reactions have been associated with high doses. There is no known potential for drug abuse for calcitonin-salmon.

Single doses of Calcitonin-Salmon Nasal Spray up to 1600 I.U., doses up to 800 I.U. per day for 3 days and chronic administration of doses up to 600 I.U. per day have been studied without serious adverse effects. A dose of 1000 I.U. of Calcitonin-Salmon injectable solution given subcutaneously may produce nausea and vomiting. A dose of Calcitonin-Salmon injectable solution of 32 I.U. per kg per day for 1 or 2 days demonstrated no additional adverse effects.

There have been no reports of hypocalcemic tetany. However, the pharmacologic actions of Calcitonin-Salmon Nasal Spray suggest that this could occur in overdose. Therefore, provisions for parenteral administration of calcium should be available for the treatment of overdose.

DOSAGE AND ADMINISTRATION

The recommended dose of Calcitonin-Salmon Nasal Spray in postmenopausal osteoporotic females is one spray (200 I.U.) per day administered intranasally, alternating nostrils daily.

Drug effect may be monitored by periodic measurements of lumbar vertebral bone mass to document stabilization of bone loss or increases in bone density. Effects of Calcitonin-Salmon Nasal Spray on biochemical markers of bone turnover have not been consistently demonstrated in studies in postmenopausal osteoporosis. Therefore, these parameters should not be solely utilized to determine clinical response to Calcitonin-Salmon Nasal Spray therapy in these patients.

Priming (Activation) of Pump

Before the first dose and administration, Calcitonin-Salmon Nasal Spray should be at room temperature. To prime the pump, the bottle should be held upright and the two white side arms of the pump depressed toward the bottle until a full spray is produced. The pump is primed once the first full spray is emitted. To administer, the nozzle should be carefully placed into the nostril with the head in the upright position, and the pump firmly depressed toward the bottle. The pump should not be primed before each daily dose.

HOW SUPPLIED

Calcitonin-Salmon Nasal Spray, USP

Available as a metered dose clear solution in a 3.7 mL fill clear glass bottle. It is available in a dosage strength of 200 I.U. per activation (0.09 mL/spray). A screw-on pump is provided. The pump, following priming, will deliver 0.09 mL of solution. Calcitonin-Salmon Nasal Spray contains 2200 I.U./mL calcitonin-salmon and is provided in an individual box containing one glass bottle and one screw-on pump (NDC 54868-6323-0).

Store and Dispense

Store unopened bottle in refrigerator between 2°C-8°C (36°F-46°F). Protect from freezing.

Store bottle in use at room temperature between 20°C-25°C (68°F-77°F) in an upright position, for up to 35 days. Each bottle contains at least 30 doses.

INFORMATION FOR THE PATIENT

Calcitonin-Salmon Nasal Spray, USP

What is CALCITONIN-SALMON Nasal Spray?

CALCITONIN-SALMON Nasal Spray is a medication used for the treatment of osteoporosis after menopause (postmenopausal osteoporosis) in women more than 5 years after menopause with low bone mass who refuse or cannot tolerate estrogens, or in whom estrogens are not an option. Patients who use CALCITONIN-SALMON Nasal Spray should be sure to ingest adequate amounts of calcium and vitamin D along with therapy.

How much calcium and vitamin D do I need each day?

When taking CALCITONIN-SALMON Nasal Spray, it is recommended that you get at least 1000 mg of calcium and 400 I.U. (international units) of vitamin D each day. Check with your doctor or healthcare provider to see if you are getting enough calcium and vitamin D in your diet. If not, he or she may recommend that you start taking calcium and vitamin D supplements.

What is osteoporosis after menopause? What causes it?

Postmenopausal osteoporosis is a condition associated with frail, brittle bones. It usually occurs when "old" bone cells are removed from bones faster than they can be replaced by "new" bone cells. As a result, bones get weak and may become susceptible to fractures.

Osteoporosis occurs most frequently in women who have gone through menopause. At menopause, a woman’s body goes through many changes, including a substantial decrease in the amount of estrogen produced. Estrogen in your body helps keep bones strong – without it, they may become weak.

Postmenopausal osteoporosis begins without notice; however, over time symptoms develop such as:

- Curved spine
- Rounded shoulders
- Loss of height

Untreated, postmenopausal osteoporosis can be painful and disabling. Some women with postmenopausal osteoporosis suffer from broken hips and fractured wrists. Fortunately, osteoporosis after menopause is treatable. Your doctor or healthcare provider can prescribe a medication, like CALCITONIN-SALMON Nasal Spray, to treat your condition.

How does CALCITONIN-SALMON Nasal Spray work?

The active ingredient in CALCITONIN-SALMON Nasal Spray is calcitonin, a man-made protein similar to one found in people, other mammals, and some types of fish and birds.

The way calcitonin affects bone is still being studied, but it is believed to work in the following ways:

- Calcitonin reduces the activity of osteoclasts [AHS-tee-oh-clasts], the cells that remove "old" bone
- Because bone building continues while bone removal is slowed down, the result is an increase in bone mass

When you spray CALCITONIN-SALMON Nasal Spray into your nostril, it is rapidly absorbed by the blood vessels lining your nasal passages. It then travels into your bloodstream and on to your bones where it works to stop bone loss and helps your bones become stronger.

How do I use CALCITONIN-SALMON Nasal Spray?

The recommended dose of CALCITONIN-SALMON Nasal Spray is one spray daily in alternated nostrils – unless directed otherwise by your healthcare provider. Start with a spray in the left nostril on your first day, followed by a spray in the right nostril on the second day. Continue to alternate nostrils every day. There are at least 30 "doses" of CALCITONIN-SALMON Nasal Spray in each bottle.

You should keep track of the number of doses used from the bottle.

After 30 doses, each spray may not deliver the correct amount of medication, even if the bottle is not completely empty.

Who should not take CALCITONIN-SALMON Nasal Spray?

CALCITONIN-SALMON Nasal Spray should not be used by patients who are allergic to the protein calcitonin-salmon, or by women who are pregnant or nursing.

You should be aware of these warnings and precautions when taking CALCITONIN-SALMON Nasal Spray.

- No formal studies designed to test drug interactions with calcitonin-salmon have been done; however, no drug interactions have been observed with the use of CALCITONIN-SALMON Nasal Spray. You should inform your doctor and pharmacist about the other prescription and nonprescription medications you are taking.
- In clinical studies, nasal symptoms occurred in approximately 9% of postmenopausal patients taking CALCITONIN-SALMON Nasal Spray. For this reason, it is recommended that a nasal examination be performed prior to the start of treatment and at any time nasal complaints occur.
- Rare instances of nasal ulceration have occurred with CALCITONIN-SALMON Nasal Spray. In some cases, your doctor may decide to temporarily discontinue treatment with CALCITONIN-SALMON Nasal Spray until symptoms subside.
- Because calcitonin-salmon is a protein, the possibility of a systemic allergic reaction exists. Patients who are allergic to calcitonin-salmon should not use CALCITONIN-SALMON Nasal Spray.
- CALCITONIN-SALMON Nasal Spray is safe to use in elderly patients. A slight increase in nasal symptoms has been observed in patients over 65 years of age; however, the symptoms are usually mild. No other unusual side effects have been seen in patients over 65 years of age.

Possible Side Effects

Most patients tolerate treatment with CALCITONIN-SALMON Nasal Spray very well; however, like all prescription drugs, CALCITONIN-SALMON Nasal Spray may cause some side effects in some people. These side effects are usually mild and generally do not lead to discontinuation of treatment with CALCITONIN-SALMON Nasal Spray. The most commonly reported side effects are:

- Nasal symptoms such as runny nose, crusting, or nasal bleeding
- Back/joint pain
- Headache

Anytime you have a medical problem you think may be related to CALCITONIN-SALMON Nasal Spray, talk to your doctor or healthcare provider.

Your doctor or pharmacist can demonstrate how to assemble, prime, and use CALCITONIN-SALMON Nasal Spray. In addition, detailed directions can be found in your CALCITONIN-SALMON Nasal Spray box. Please read them carefully before assembling and using the spray.

This medication is prescribed for a particular condition. Do not use it for another condition or give the drug to others. Keep CALCITONIN-SALMON Nasal Spray and all medicines out of reach of children. This leaflet provides a summary of information about CALCITONIN-SALMON Nasal Spray. If you have any questions or concerns about either CALCITONIN-SALMON Nasal Spray or osteoporosis, talk to your doctor. In addition, talk to your pharmacist or other healthcare provider.

HOW TO ASSEMBLE AND USE

CALCITONIN-SALMON NASAL SPRAY, USP

One Spray, Once a Day

BEFORE USING CALCITONIN-SALMON NASAL SPRAY

This package contains one bottle of Calcitonin-Salmon Nasal Spray and one screw on pump.

Important Facts About Your Medication

- The bottle contains the proper amount of medication — be aware that the entire bottle will not be filled with liquid.
- Before opening and assembling your medication bottle, keep it in your refrigerator between 2°C to 8°C (36°F to 46°F). Do not freeze.
- After opening and assembling a new medication bottle, keep it at room temperature between 20°C to 25°C (68°F to 77°F) in an upright position.

HOW TO USE CALCITONIN-SALMON NASAL SPRAY

Putting the Nasal Spray Pump Unit Together

1. If your bottle and pump unit were already assembled by your pharmacist, go to step 6. If not, remove the bottle from your refrigerator and allow it to reach room temperature before assembling.

2. Keeping the bottle upright, unscrew the white cap.

3. Remove the pump from the plastic protection bag.

4. Holding the bottle upright, insert the nasal spray pump unit into the bottle. Then turn the pump clockwise, and tighten it until it is securely fastened to the bottle.

Note: Do not depress pump when it is not attached to the bottle.

5. Holding the bottle upright with your index finger on top of one of the two side arms of the pump, gently remove the clear protective cap from the top of the nozzle.

Priming a New Bottle

6. To ensure proper delivery of medication, a newly opened and assembled bottle must be primed before you use it for the first time.

If your pharmacist assembled the unit for you, check to see if it has already been primed by pumping the unit once. If a full spray is emitted, the unit has already been primed. If no spray is emitted, you must prime the unit. Holding the bottle upright with your index and middle fingers on the two side arms of the pump, and your thumb on the bottom of the bottle, press the arms down fully until you see a full spray. Now the nasal spray is ready for use.

Do not re-prime the pump before each daily use because this will waste your medication.

Using the Medication

7. The recommended dose of Calcitonin-Salmon Nasal Spray is one spray once a day in one nostril.

Keep your head upright and carefully place the nozzle in one nostril.

Tilt the bottle until it is in a straight line with the nasal passage.

Firmly press down on the pump once to spray the medication into your nose. It is not necessary to inhale while this is being done. Please note: Because the mist is so fine, you may not feel it inside your nose. Also, some medication may drip out of your nose. However, in either case, the medication is absorbed. IMPORTANT: Do not "test" the spray unit or prime it before you use your daily dose because this will waste your medication.

Cleaning the Pump

Once or twice a week, wipe the nozzle with a clean, damp cloth. Dry the nozzle before replacing the dust cap

Storing the Unit

8. Holding the bottle with two fingers under the two side arms of the pump, gently replace the protective cap on the nasal spray unit. Be careful not to depress the pump while this is being done. Once the pump is primed, the unit must be kept at room temperature between 20°C to 25°C (68°F to 77°F) in the upright position until the medication is finished.

IMPORTANT

- Do not refrigerate the unit between doses
- Do not store the unit on its side

Bottles left at room temperature (opened or unopened) for more than 35 days must be discarded.

Refrigerated bottles are good until the expiration date stamped on the bottle and box.

Alternate Nostrils Daily

The first day, start with one spray in the left nostril. The next day, use one spray in the right nostril, and so on.

It is important to receive the correct daily amount of calcium and vitamin D, as directed by your healthcare provider.

IMPORTANT

- Use Calcitonin-Salmon Nasal Spray daily.

To ensure proper treatment, it is important to use your Calcitonin-Salmon Nasal Spray daily even if you have no symptoms of postmenopausal osteoporosis.

A single spray of Calcitonin-Salmon Nasal Spray, USP contains one daily dose, which is 200 I.U. of calcitonin-salmon. The fine mist is actually 0.09 mL (milliliter) of solution. Your bottle of Calcitonin-Salmon Nasal Spray contains at least 30 doses. Priming the pump as described in step 6 does not alter the total number of doses available in a bottle of Calcitonin-Salmon Nasal Spray. The bottle need only be primed once after assembly. Do not reprime or "test spray" your bottle before you use your daily dose of Calcitonin-Salmon Nasal Spray. This will waste your medication.

Please see your healthcare provider for complete product information for Calcitonin-Salmon Nasal Spray.

Distributed by:

Par Pharmaceutical Companies, Inc.

Spring Valley, NY 10977

Revised: 02/11 OS161-01-1-03

Additional barcode label applied by:
Physicians Total Care, Inc.
Tulsa, Oklahoma 74146